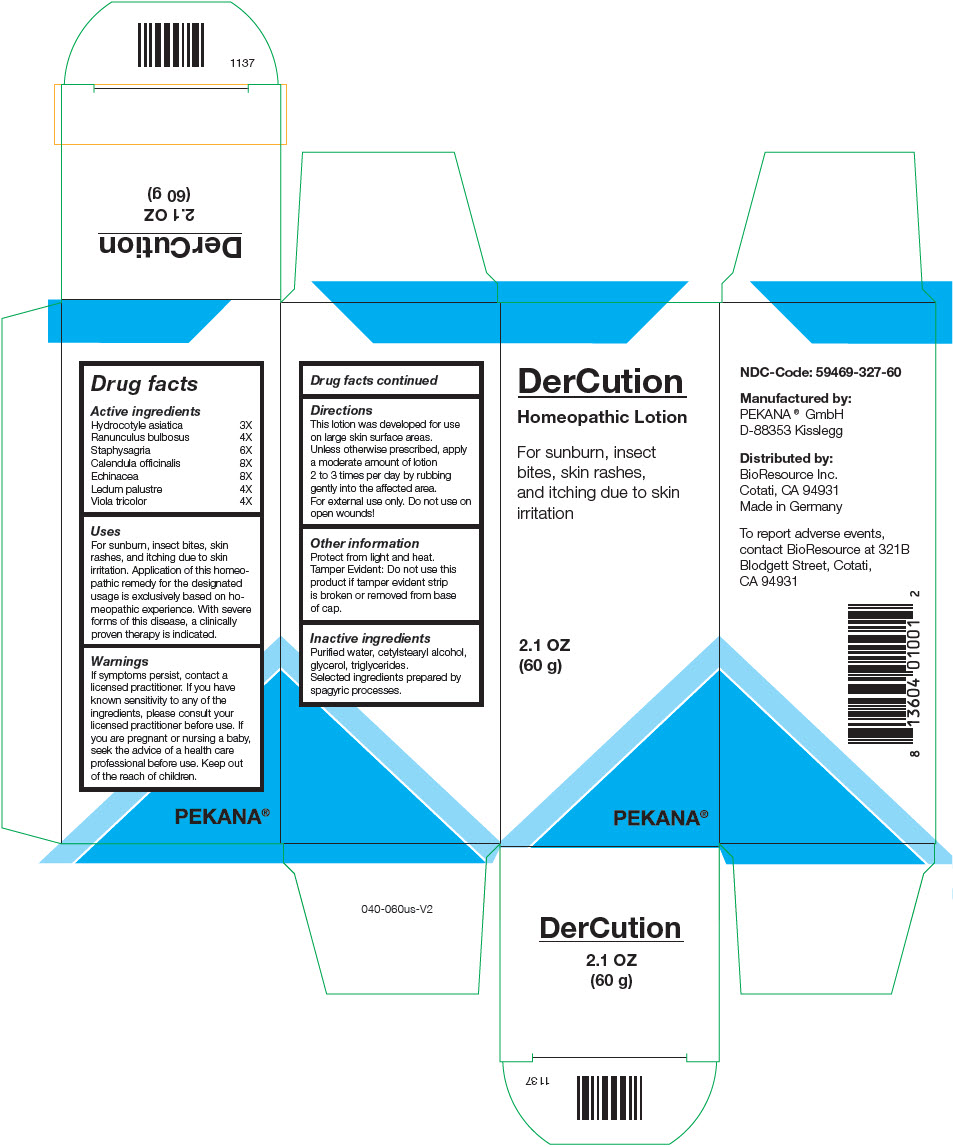 DRUG LABEL: DerCution
NDC: 59469-327 | Form: LOTION
Manufacturer: PEKANA Naturheilmittel GmbH
Category: homeopathic | Type: HUMAN OTC DRUG LABEL
Date: 20230111

ACTIVE INGREDIENTS: CENTELLA ASIATICA WHOLE 3 [hp_X]/100 g; RANUNCULUS BULBOSUS WHOLE 4 [hp_X]/100 g; DELPHINIUM STAPHISAGRIA SEED 6 [hp_X]/100 g; CALENDULA OFFICINALIS FLOWERING TOP 8 [hp_X]/100 g; ECHINACEA, UNSPECIFIED 8 [hp_X]/100 g; RHODODENDRON TOMENTOSUM LEAFY TWIG 4 [hp_X]/100 g; VIOLA TRICOLOR WHOLE 4 [hp_X]/100 g
INACTIVE INGREDIENTS: MEDIUM-CHAIN TRIGLYCERIDES; CETOSTEARYL ALCOHOL; GLYCERIN; WATER

DerCution

Drug facts

Active ingredients
Hydrocotyle asiatica | 3X
Ranunculus bulbosus | 4X
Staphysagria | 6X
Calendula officinalis | 8X
Echinacea | 8X
Ledum palustre | 4X
Viola tricolor | 4X

Uses

PURPOSE

For sunburn, insect bites, skin rashes, and itching due to skin irritation. Application of this homeopathic remedy for the designated usage is exclusively based on homeopathic experience. With severe forms of this disease, a clinically proven therapy is indicated.

Warnings

If symptoms persist, contact a licensed practitioner. If you have known sensitivity to any of the ingredients, please consult your licensed practitioner before use. If you are pregnant or nursing a baby, seek the advice of a health care professional before use.

Keep out of the reach of children.

Directions

This lotion was developed for use on large skin surface areas.

Unless otherwise prescribed, apply a moderate amount of lotion 2 to 3 times per day by rubbing gently into the affected area.

For external use only. Do not use on open wounds!

Other information

Protect from light and heat.

Tamper Evident: Do not use this product if tamper evident strip is broken or removed from base of cap.

Inactive ingredients

Purified water, cetylstearyl alcohol, glycerol, triglycerides. Selected ingredients prepared by spagyric processes.

QUESTIONS

To report adverse events, contact BioResource at 321B Blodgett Street, Cotati, CA 94931

Manufactured by:
PEKANA® GmbH
D-88353 Kisslegg

Distributed by:
BioResource Inc.
Cotati, CA 94931

PRINCIPAL DISPLAY PANEL - 60 g Bottle Box

DerCution
Homeopathic Lotion

For sunburn, insect
bites, skin rashes,
and itching due to skin
irritation

2.1 OZ
(60 g)

PEKANA®